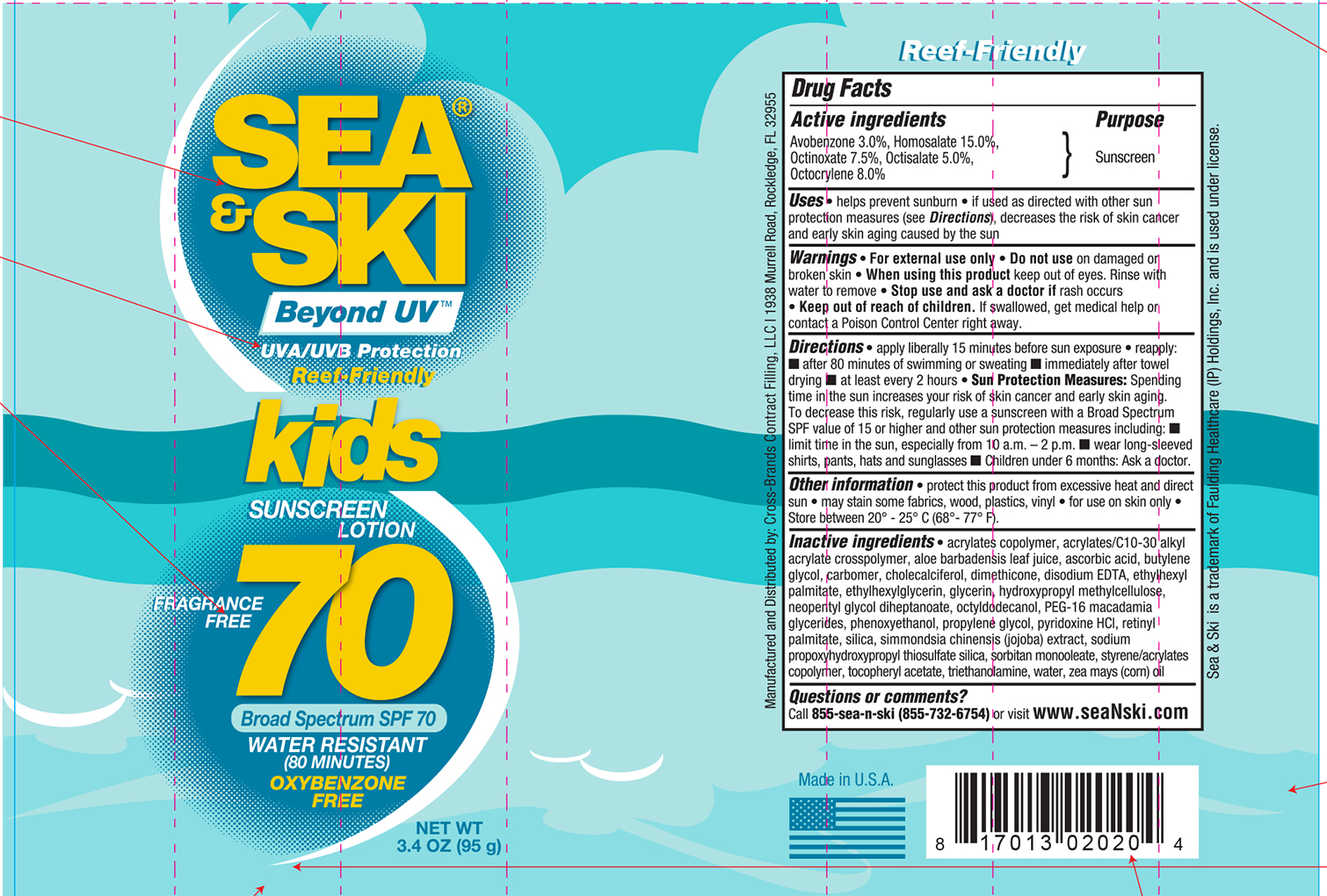 DRUG LABEL: Sea and Ski SPF 70 Kids
NDC: 73440-2020 | Form: LOTION
Manufacturer: Cross-Brands Contract Filling
Category: otc | Type: HUMAN OTC DRUG LABEL
Date: 20210219

ACTIVE INGREDIENTS: OCTINOXATE 7.13 g/95 g; OCTISALATE 4.75 g/95 g; OCTOCRYLENE 7.6 g/95 g; AVOBENZONE 2.85 g/95 g; HOMOSALATE 14.25 g/95 g
INACTIVE INGREDIENTS: WATER 44.6 g/95 g

Sea&Ski SPF 70 Kids 3.4oz